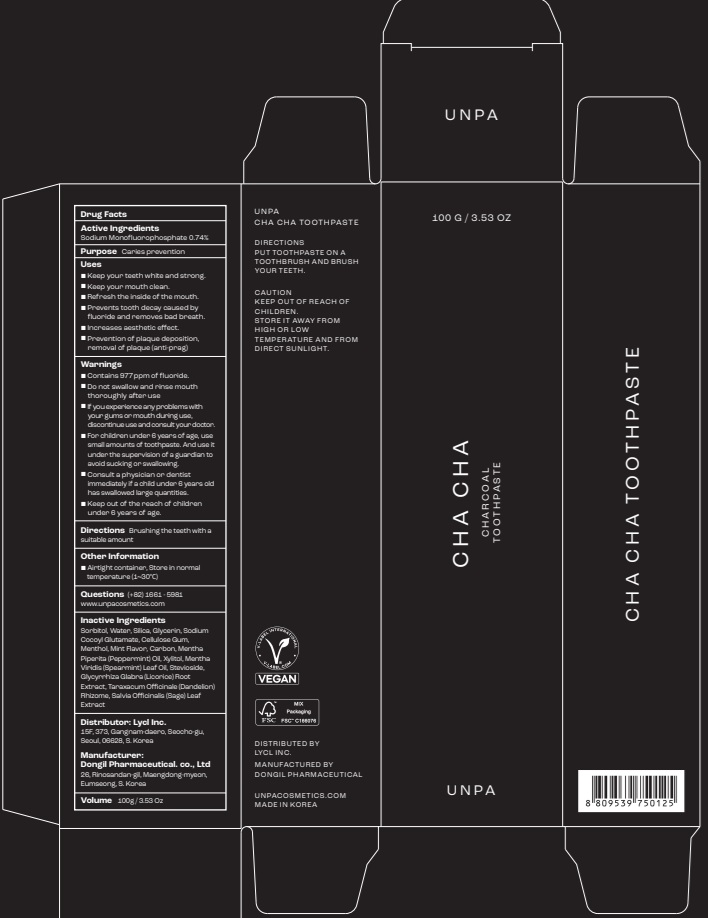 DRUG LABEL: UNPA CHA CHA TOOTHPASTE
NDC: 73242-1111 | Form: PASTE
Manufacturer: DONG IL PHARMS CO.,LTD
Category: otc | Type: HUMAN OTC DRUG LABEL
Date: 20250926

ACTIVE INGREDIENTS: SODIUM MONOFLUOROPHOSPHATE 0.74 g/100 g
INACTIVE INGREDIENTS: SORBITOL; SILICON DIOXIDE; WATER

Active ingredient(s)

Sodium Monofluorophosphate 0.74%

Purpose

Caries prevention

Uses

■ Keep your teeth white and strong.
■ Keep your mouth clean.
■ Refresh the inside of the mouth.
■ Prevents tooth decay caused by fluoride and removes bad breath.
■ Increases aesthetic effect.
■ Prevention of plaque deposition, removal of plaque (anti-prag)

Warnings

■ Contains 977ppm of fluoride.
■ Do not swallow and rinse mouth thoroughly after use
■ If you experience any problems with your gums or mouth during use, discontinue use and consult your doctor.
■ For children under 6 years of age, use small amounts of toothpaste. And use it under the supervision of a guardian to avoid sucking or swallowing.
■ Consult a physician or dentist immediately if a child under 6 years old has swallowed large quantities.
■ Keep out of the reach of children under 6 years of age.

KEEP OUT OF REACH OF CHILDREN

■ Keep out of the reach of children under 6 years of age.

Directions

■ Brushing the teeth with a suitable amount

Other Information

■ Airtight container, Store in normal temperature (1~30℃)

Inactive ingredients

Sorbitol, Water, Silica, Glycerin, Sodium Cocoyl Glutamate, Cellulose Gum, Menthol, Mint Flavor, Carbon, Mentha Piperita (Peppermint) Oil, Xylitol, Mentha Viridis (Spearmint) Leaf Oil, Stevioside, Glycyrrhiza Glabra (Licorice) Root Extract, Taraxacum Officinale (Dandelion) Rhizome, Salvia Officinalis (Sage) Leaf Extract